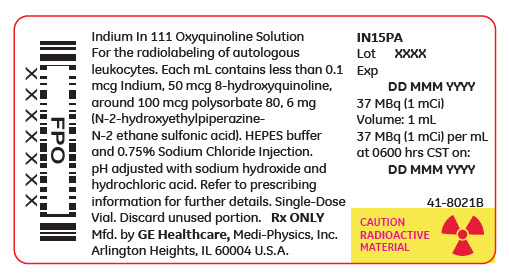 DRUG LABEL: Indium in 111 Oxyquinoline
NDC: 17156-021 | Form: SOLUTION
Manufacturer: Medi-Physics Inc. dba GE Healthcare.
Category: prescription | Type: HUMAN PRESCRIPTION DRUG LABEL
Date: 20240110

ACTIVE INGREDIENTS: Indium In-111 Oxyquinoline 1 ug/1 mL
INACTIVE INGREDIENTS: Polysorbate 80 100 ug/1 mL

INDIUM IN 111
OXYQUINOLINE SOLUTION, for radiolabeling

Rx ONLY

Diagnostic—For intravenous use
Single-dose vial

DESCRIPTION

Indium In 111 Oxyquinoline (oxine) Solution is a diagnostic radiopharmaceutical intended for radiolabeling autologous leukocytes. It is supplied as a sterile, non-pyrogenic, isotonic aqueous solution with a pH range of 6.5 to 7.5 [sodium hydroxide and hydrochloric acid may be used to adjust the pH]. Each mL of the solution contains 37 MBq, 1 mCi of indium In 111 [no carrier added, >1.85 GBq/mcg indium (>50 mCi/mcg indium)] at calibration time, 50 mcg oxyquinoline, 100 mcg polysorbate 80, and 6 mg of HEPES (N-2-hydroxyethyl-piperazine-N'-2-ethane sulfonic acid) buffer in 0.75% Sodium Chloride Solution. The drug is intended to be used as a single-dose vial and contains no bacteriostatic agent. The radionuclidic impurity limit for indium 114m is not greater than 37 kBq, 1 µCi of indium 114m per 37 MBq, 1 mCi of indium In 111 at the time of calibration. The radionuclidic composition at expiration time is not less than 99.75% of indium In 111 and not more than 0.25% of indium In 114m/114.

Chemical name: Indium In 111 Oxyquinoline.

The precise structure of the indium In 111 oxyquinoline complex is unknown at this time. The empirical formula is (C9H6NO)3 In 111.

PHYSICAL CHARACTERISTICS

Indium In 111 decays by electron capture with a physical half-life of 67.9 hours (2.8 days). The energies of the photons that are useful for detection and imaging studies are listed in Table 1.

Table 1. Principal Radiation Emission Data [Kocher, David C., "Radioactive Decay Data Tables", DOE/TIC-11026, 115 (1981).]
Radiation | Mean %/ Disintegration | Mean Energy (keV)
Gamma 2 | 90.2 | 171.3
Gamma 3 | 94 | 245.4

EXTERNAL RADIATION

The exposure rate constant for 37 MBq, 1 mCi indium In 111 is 8.3 × 10^-4 C/kg/h (3.21 R/h) at 1 cm. The first half value thickness of lead (Pb) for indium In 111 is 0.023 cm. A range of values for the relative attenuation of the radiation emitted by this radionuclide that results from the interposition of various thicknesses of Pb is shown in Table 2. For example, the use of 0.834 cm of lead will decrease the external radiation exposure by a factor of about 1,000.

Table 2. Radiation Attenuation by Lead Shielding [Data supplied by Oak Ridge Associated Universities, Radiopharmaceutical Internal Dose Information Center, 1984.]
Shield Thickness (Pb) cm | Coefficient of Attenuation
0.023 | 0.5
0.203 | 10^-1
0.513 | 10^-2
0.834 | 10^-3
1.12 | 10^-4

These estimates of attenuation do not take into consideration the presence of longer-lived contaminants with higher energy photons, namely indium In 114m/114.

To allow correction for physical decay of indium In 111, the fractions that remain at selected intervals before and after the time of calibration are shown in Table 3.

Table 3. Physical Decay Chart for Indium In 111, Half-life 67.9 hours
Day | Fraction Remaining | Day | Fraction Remaining
-2 | 1.632 | 2 | 0.613
-1 | 1.278 | 3 | 0.480
0 [Calibration Time] | 1 | 4 | 0.375
1 | 0.783 | 5 | 0.294

CLINICAL PHARMACOLOGY

Indium forms a saturated (1:3) complex with oxyquinoline. The complex is neutral and lipid-soluble, which enables it to penetrate the cell membrane. Within the cell, indium becomes firmly attached to cytoplasmic components; the liberated oxyquinoline is released by the cell. It is thought likely that the mechanism of labeling cells with Indium In 111 Oxyquinoline Solution involves an exchange reaction between the oxyquinoline carrier and subcellular components which chelate indium more strongly than oxyquinoline. The low stability constant of the oxyquinoline complex, estimated at approximately 10, supports this theory.

Following the recommended leukocyte cell labeling procedure, approximately 77% of the added indium In 111 oxyquinoline is incorporated in the resulting cell pellet (which represents approximately 3 to 4 × 10^8 WBC).

Cell clumping can occur and was found in about one fifth of the leukocyte preparations examined. The presence of red blood cells or plasma will lead to reduced leukocyte labeling efficiency. Transferrin in plasma competes for indium In 111 oxyquinoline.

After injection of labeled leukocytes into normal volunteers, about 30% of the dose is taken up by spleen and 30% by liver, reaching a plateau at 2 to 48 hours after injection. No significant clearance of radioactivity is observed at 72 hours in these two organs. Pulmonary uptake is 4 to 7.5% at 10 minutes but is lost rapidly; pulmonary radioactivity is usually visible in scans only up to about 4 hours after injection.

The human biodistribution studies in three normal subjects injected with indium In 111 oxyquinoline labeled leukocytes indicate a biexponential disappearance of indium In 111 from the blood when monitored for up to 72 hours. Between 9.5 to 24.4% of the injected dose remains in whole blood and clears with a biological half-time of 2.8 to 5.5 hours. The remainder (13 to 18%) clears from blood with a biological half-time of 64 to 116 hours.

Elimination from the body of injected indium In 111 oxyquinoline is probably mainly through decay to stable cadmium since only a negligible amount (less than 1%) of the dose is excreted in feces and urine in 24 hours.

Clearance from whole blood and biological distribution can vary considerably with the individual recipient, the condition of the injected cells and labeling techniques used.

Release of radioactivity from the labeled cells is about 3% at 1 hour and 24% at 24 hours.

Clearance from liver and spleen, for the purpose of calculating the radiation dose, is assumed to be equal to the physical half-life of indium In 111 (67.9 hours).

INDICATIONS AND USAGE

Indium In 111 Oxyquinoline Solution is indicated for radiolabeling autologous leukocytes.

Indium In 111 oxyquinoline labeled leukocytes may be used as an adjunct in the detection of inflammatory processes to which leukocytes migrate, such as those associated with abscesses or other infection, following reinjection and detection by appropriate imaging procedures. The degree of accuracy may vary with labeling techniques and with the size, location and nature of the inflammatory process.

Indium In 111 oxyquinoline labeled leukocyte imaging is not the preferred technique for the initial evaluation of patients with a high clinical probability of an abscess in a known location. Ultrasound or computed tomography may provide a better anatomical delineation of the infectious process and information may be obtained more quickly than with labeled leukocytes. If localization by these techniques is successful, labeled leukocytes should not be used as a confirmatory procedure. If localization or diagnosis by these methods fails or is ambiguous, indium In 111 oxyquinoline labeled leukocyte imaging may be appropriate.

CONTRAINDICATIONS

None known.

WARNINGS

The content of the vial of Indium In 111 Oxyquinoline Solution is intended only for use in the preparation of indium In 111 oxyquinoline labeled autologous leukocytes, and is not to be administered directly. Autologous leukocyte labeling is not recommended in leukopenic patients because of the small number of available leukocytes.

Due to radiation exposure, indium In 111 oxyquinoline labeled leukocytes could cause fetal harm when administered to pregnant women. If this radiopharmaceutical is used during pregnancy, the patient should be informed of the potential hazard to the fetus.

Indium In 111 oxyquinoline labeled autologous leukocytes should be used only when the benefit to be obtained exceeds the risks involved in children under eighteen years of age owing to the high radiation burden and the potential for delayed manifestation of long-term adverse effects.

PRECAUTIONS

Clumping of cells may produce focal accumulations of radioactivity in lungs which do not wash out in 24 hours and thus may lead to false positive results. This phenomenon can be detected by imaging the chest immediately after injection.

The normally high uptake of indium In 111 oxyquinoline labeled leukocytes by spleen and liver may mask inflammatory lesions in these organs. Labeled leukocytes have been observed to accumulate in the colon and accessory spleens of patients with or without disease.

Chemotaxis of granulocytes deteriorates during storage and loss of chemotaxis may cause false negative scans. The spontaneous release of indium In 111 has been reported to range from about 3% at one hour to 24% at 24 hours [ten Berge, R.J.M., Natarajan, A.T., Hardeman, M.R., et al, Labeling with indium In 111 has detrimental effects on human lymphocytes, Journal of Nuclear Medicine, 24, 615-620 (1983)]. The maximum amount of time recommended between drawing the blood and reinjection should not exceed 5 hours. It is recommended that the labeled cells be used within one hour of preparation, if possible and in no case more than three hours after preparation.

Plasma and red cell contamination impairs labeling efficiency of leukocytes. Hemolyzed blood in labeled leukocytes may produce heart pool activity and should be avoided.

Cell aggregates of various degrees have been reported. Cell labeling techniques and standing of cell preparation may be contributing factors.

Nuclear medicine procedures involving withdrawal and reinjection of blood have the potential for transmission of blood borne pathogens. Procedures should be implemented to avoid administration errors and viral contamination of personnel during blood product labeling. A system of checks similar to the ones used for administering blood transfusions should be routine.

General

Strict aseptic techniques should be used to maintain sterility throughout the procedures for using this product.

Do not use after the expiration time and date (5 days after calibration time) stated on the label.

The contents of the vial are radioactive. Adequate shielding of the preparation must be maintained at all times.

Indium In 111 Oxyquinoline Solution, like other radioactive drugs, must be handled with care and appropriate safety measures should be used to minimize radiation exposure to clinical personnel. Care should also be taken to minimize radiation exposure to the patient consistent with proper patient management.

Radiopharmaceuticals should be used only by physicians who are qualified by training and experience in the safe use and handling of radionuclides and whose experience and training have been approved by the appropriate governmental agency authorized to license the use of radionuclides.

Carcinogenesis, Mutagenesis, Impairment of Fertility

Although earlier studies suggested that oxyquinoline (oxine) might have carcinogenic potential, recent studies have found no evidence of carcinogenicity in either rats or mice given oxyquinoline in feed at concentrations of 1,500 or 3,000 ppm for 103 weeks.

It has been reported [ten Berge, R.J.M., Natarajan, A.T., Hardeman, M.R., et al, Labeling with indium In 111 has detrimental effects on human lymphocytes, Journal of Nuclear Medicine, 24, 615-620 (1983)] that human lymphocytes labeled with recommended concentrations of indium In 111 oxyquinoline showed chromosome aberrations consisting of gaps, breaks and exchanges that appear to be radiation induced. At 555 kBq/10^7, 15 µCi/10^7 lymphocytes 93% of the cells were reported to be abnormal. The oncogenic potential of such lymphocytes has not been studied. It has been reported that the radiation dose to 10^8 leukocytes is 9 × 10^4 mGy (0.9 × 10^4 rads) from 18.5 MBq, 500 µCi [Goodwin, David A., Cell labeling with oxine chelates of radioactive metal ions: Techniques and clinical implications, Journal of Nuclear Medicine, 19, 557-559 (1978)].

Studies have not been performed to evaluate whether indium In 111 oxyquinoline affects fertility in male or female laboratory animals or humans.

Pregnancy

Animal reproduction studies have not been conducted with indium In 111 oxyquinoline labeled leukocytes. It is also not known whether indium In 111 oxyquinoline labeled leukocytes can cause fetal harm when administered to a pregnant woman or can affect reproduction capacity.

However, Indium Nitrate, a closely related compound, was teratogenic and embryopathic in hamsters. Indium In 111 oxyquinoline labeled leukocytes should be given to a pregnant woman only if clearly needed.

Ideally, examinations using radiopharmaceuticals, especially those elective in nature, in women of childbearing capability should be performed during the first few (approximately ten) days following the onset of menses.

Nursing Mothers

It is reported that indium 111 is secreted in human milk following administration of indium In 111 labeled leukocytes. Therefore, formula feedings should be substituted for breast feedings.

Pediatric Use

Safety and effectiveness in pediatric patients below age 18 have not been established (See Warnings).

Geriatric Use

Other reported clinical experience has not identified differences in responses between the elderly and younger patients. In general, dose selection for an elderly patient should be cautious usually starting at the low end of the dosing range, reflecting the greater frequency of decreased hepatic, renal, or cardiac function, and of concomitant disease or other drug therapy.

ADVERSE REACTIONS

Sensitivity reactions (urticaria) have been reported. The presence of fever may mask pyrogenic reactions from indium In 111 oxyquinoline labeled leukocytes. The possibility of delayed adverse reactions has not been studied.

DOSAGE AND ADMINISTRATION

The recommended adult (70 kg) dose of indium In 111 oxyquinoline labeled autologous leukocytes is 7.4 to 18.5 MBq, 200 to 500 µCi. Indium In 111 Oxyquinoline Solution is intended for the radiolabeling of autologous leukocytes. The indium In 111 oxyquinoline labeled autologous leukocytes are administered intravenously.

Imaging is recommended at approximately 24 hours post injection. Typically, anterior and posterior views of the chest, abdomen and pelvis should be obtained with other views as required.

Aseptic procedures and a shielded syringe should be employed in the withdrawal of Indium In 111 Oxyquinoline Solution from the vial. Similar procedures should be employed during the labeling procedure and the administration of the labeled leukocytes to the patient. The user should wear waterproof gloves during the entire procedure. The patient's dose should be measured by a suitable radioactivity calibration system immediately before administration. At this time, the leukocyte preparation should be checked for gross clumping and red blood cell contamination.

RADIATION DOSIMETRY

The estimated absorbed radiation doses to an adult patient weighing 70 kg from an intravenous dose of 18.5 MBq, 500 µCi of indium In 111 oxyquinoline labeled leukocytes including contributions from indium In 114m/114 as a radionuclidic impurity are shown in Table 4.

Table 4. Radiation Dose Estimate in a 70 kg Human for 18.5 MBq, 500 µCi at Expiry of Indium In 111 (99.75%) Oxyquinoline Labeled Leukocytes with Indium In 114m/114 (0.25%)
Organ | mGy/18.5 MBq In 111 | Rads/500 µCi In 111
Spleen | 130 | 13
Liver | 19 | 1.9
Red Marrow | 13 | 1.3
Skeleton | 3.64 | 0.364
Testes | 0.1 | 0.01
Ovaries | 1.9 | 0.19
Total Body | 3.1 | 0.31
Organ | mGy/46.25 kBq In 114m/114 | Rads/1.25 µCi In 114m/114
Spleen | 70 | 7
Liver | 7.1 | 0.71
Red Marrow | 6.9 | 0.69
Skeleton | 0.85 | 0.085
Testes | 0.04 | 0.004
Ovaries | 0.06 | 0.006
Total Body | 0.6 | 0.06
Organ | Total Dose in mGy | Total Dose in Rads
Spleen | 200 | 20
Liver | 26.6 | 2.66
Red Marrow | 19.9 | 1.99
Skeleton | 4.5 | 0.45
Testes | 0.14 | 0.014
Ovaries | 2 | 0.2
Total Body | 3.7 | 0.37
Assumptions: 30% to spleen, 30% to liver, 34% to red marrow, 6% to remainder of body, with no excretion.

The dose of radiation absorbed by the organs will vary with the distribution of the blood cells in the organs, which in turn will depend on the predominance of the cell types labeled and their condition.

LABELING PROCEDURE

Sterile technique must be used throughout. It is important that all equipment used for the preparation of reagents be thoroughly cleaned to assure the absence of trace metal impurities. The user should wear waterproof gloves during the handling and administration procedure.

1. The following equipment is recommended:
  One (1) 60 mL or two (2) 30 mL sterile disposable plastic syringes with a 19 or 20 gauge needle (NOTE: Do not use a smaller gauge needle).
  Ring stand and clamp(s).
  Three (3) 50 mL sterile conical plastic centrifuge tubes with screw caps. Label each set with patient ID and "WBC", "LPP" and "Wash" respectively (NOTE: 3 centrifuge tubes per patient).
  Clinical Centrifuge with horizontal, 4 place rotor or equivalent.
  Sodium Chloride (0.9%) Injection, USP.
  Three (3) disposable 5 or 10 mL syringes and 19 gauge needles.
  Syringe shield to dispense Indium In 111 Oxyquinoline Solution.
  A dose calibrator.
  Butterfly catheter infusion set.
  Test tube rack.
  Lab timer.
  10 mL syringe with a 19 gauge or 20 gauge needle.
  19 gauge needle with filter (optional).
2. Withdraw from the patient 30 to 50 mL blood [preferably fifty (50) mL] using aseptic venipuncture technique using the 60 mL syringe fitted with a 19 gauge or 20 gauge needle and containing approximately 1,000 to 1,500 units heparin in 1 to 2 mL. Blood withdrawal should be smooth and slow so as not to produce bubbles or foaming.
3. Remove and dispose of the needle and replace with a syringe cap. Gently mix the contents of the syringe and label with the patient's ID, date and time.
4. Upon receipt of the full syringe for processing, the contents should again be gently mixed.
5. Clamp the syringe barrel to the ring stand in an upright (needle side up) position and tilt the syringe 10 to 20 degrees from its position perpendicular to the bench.
6. Allow the red cells to sediment 30 to 60 minutes, depending upon when the supernatant [leukocyte rich plasma (LRP)] looks clear of red blood cells.
7. Replace the syringe cap with an infusion set.
8. Collect the plasma (LRP) in the centrifuge tube marked "WBC" by expressing the LRP through the catheter tubing making sure not to get any red cells into the WBC tube.
9. Immediately centrifuge the capped WBC tube at 400 to 450 g for 5 minutes.
10. Transfer the supernatant to the leukocyte poor plasma (LPP) tube leaving behind 0.5 to 1 mL supernatant to cover the white cell button (NOTE: the button often contains a small number of red cells and may appear red).
11. Wash the white cell button with 4 to 6 mL Sodium Chloride (0.9%) Injection, USP. Resuspend the button by gentle swirling.
12. Centrifuge the capped WBC tube at 400 to 450 g for 5 minutes (alternatively, 150 g for 8 minutes) and discard all but 0.5 to 1 mL of the supernate to cover the cells.
13. Add 5 mL Sodium Chloride (0.9%) Injection, USP. Resuspend the cells by gentle swirling.
14. With the shielded syringe, draw up approximately 22.2 MBq, 600 µCi Indium In 111 Oxyquinoline Solution. Check the amount of radioactivity in a dose calibrator set for indium In 111 and record for labeling efficiency calculations.
  Parenteral drug products should be inspected visually for particulate matter and discoloration before administration.
15. In several additions, add the Indium In 111 Oxyquinoline Solution to the WBC tube, gently swirling after each addition.
16. Set the lab timer for 15 minutes and allow the capped WBC tube to incubate. Swirl the cell preparation several times during the incubation.
17. With a sterile plastic syringe, add half of the saved LPP (or about 8 mL) from the LPP tube. Cap and gently swirl the contents of WBC tube to resuspend the cells.
18. Centrifuge the WBC tube at 450 g for 5 minutes (or 150 g for 8 minutes). Decant supernatant into the wash tube leaving behind about 0.5 mL of the supernate to cover the cells.
19. Assay the activity in the WBC tube and in the wash tube in a dose calibrator and record.
20. With a sterile plastic syringe add the remaining LPP to the cell button and gently resuspend by swirling. With a sterile syringe fitted with a 19 gauge needle, resuspend the cells by drawing the cells up into the syringe and expressing the suspension against the tube gently once or twice. Alternatively, draw up the cells into a syringe fitted with the filtered 19 gauge needle, and replace the needle with an unfiltered 19 or 20 gauge needle.
21. Reserve in the WBC tube a minimum amount of white cell suspension for a WBC count. A microscopic examination should also be completed to observe for clumping. Draw up the patient's dose (7.4 to 18.5 MBq, 200 to 500 µCi) and check the syringe in the dose calibrator. Record the measurement.

QUALITY CONTROL

It is generally advantageous to record any observations on cell abnormalities (e.g., cell clumping). A trypan blue exclusion test may also be performed.

It is recommended that the preparation be used within one hour of labeling (See Precautions).

HOW SUPPLIED

Indium In 111 Oxyquinoline Solution is supplied in a 1 mL single-dose vial containing 37 MBq, 1 mCi per mL aqueous solution at the calibration date stated on the label. Vials are packaged in individual lead shields.

NDC 17156-021-01

The contents of the vial are radioactive and adequate shielding and handling precautions must be maintained.

This preparation is approved for use by persons licensed by the Illinois Emergency Management Agency pursuant to 32 IL. Adm. Code Section 330.260(a) and 335.4010 or equivalent licenses of the Nuclear Regulatory Commission or an Agreement State.

SPECIAL HANDLING AND STORAGE

Indium In 111 Oxyquinoline Solution should be stored at a temperature between 15° to 25°C (59° to 77°F).

Indium In 111 oxyquinoline labeled autologous leukocytes should preferably be reinjected within one hour of labeling. The labeled cells may be stored at a temperature between 15° to 25°C (59° to 77°F) for up to three hours following completion of the cell labeling procedure. Reinjection of indium In 111 oxyquinoline labeled autologous leukocytes more than 5 hours after initial blood drawing is not recommended.

Sterile technique must be used throughout the collection, labeling and re-injection procedures.

Manufactured by:
GE Healthcare
Medi-Physics, Inc.
Arlington Heights, IL 60004 U.S.A.

Customer Service: 1-800-292-8514
Professional Services: 1-800-654-0118

GE and the GE Monogram are trademarks of
General Electric Company or one of its subsidiaries.

© 2022 General Electric Company - All rights
reserved.

43-8021B
Revised May 2022

PRINCIPAL DISPLAY PANEL - 1 mL Vial Label

Indium In 111 Oxyquinoline Solution
For the radiolabeling of autologous
leukocytes. Each mL contains less than 0.1
mcg Indium, 50 mcg 8-hydroxyquinoline,
around 100 mcg polysorbate 80, 6 mg
(N-2-hydroxyethylpiperazine-
N-2 ethane sulfonic acid). HEPES buffer
and 0.75% Sodium Chloride Injection.
pH adjusted with sodium hydroxide and
hydrochloric acid. Refer to prescribing
information for further details. Single-Dose
Vial. Discard unused portion.

Rx ONLY
Mfd. by GE Healthcare, Medi-Physics, Inc.
Arlington Heights, IL 60004 U.S.A.

IN15PA
Lot XXXX
Exp
DD MMM YYYY
37 MBq (1 mCi)
Volume: 1 mL
37 MBq (1 mCi) per mL
at 0600 hrs CST on:
DD MMM YYYY

41-8021B

CAUTION
RADIOACTIVE
MATERIAL